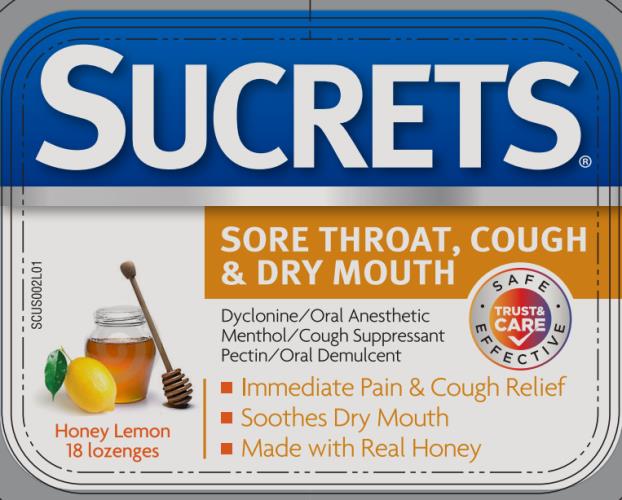 DRUG LABEL: Sucrets
NDC: 63736-567 | Form: LOZENGE
Manufacturer: Insight Pharmaceuticals LLC
Category: otc | Type: HUMAN OTC DRUG LABEL
Date: 20240320

ACTIVE INGREDIENTS: DYCLONINE HYDROCHLORIDE 2 mg/1 1; MENTHOL 5 mg/1 1; PECTIN 6 mg/1 1
INACTIVE INGREDIENTS: CORN SYRUP; FD&C YELLOW NO. 5; FD&C YELLOW NO. 6; HONEY; LEMON OIL; PROPYLENE GLYCOL; SUCROSE; TARTARIC ACID; WATER

Sucrets Medicated Honey Lemon 63736-567

SUCRETS SORE THROAT, COUGH & DRY MOUTH

Purpose

Active ingredients (per lozenge) | Purpose
Dyclonine hydrochloride 2 mg | Oral anesthetic/Analgesic
Menthol 5 mg | Cough suppressant
Pectin 6 mg | Demulcent

Uses

temporarily relieves:

- occasional minor irritation, pain, sore throat, and sore mouth
- cough associated with a cold or inhaled irritants
- for protection of irriated areas in sore mouth and throat

Warnings

Sore throat warning: if sore throat is severe, persists for more than 2 days, is accompanied by fever, headache, rash, swelling, nausea, or vomiting, consult a doctor promptly.

Ask a doctor before use if you have

- cough that lasts or is chronic such as occurs with smoking, asthma, emphysema
- cough that occurs with too much phlegm (mucus)

Stop use and ask a doctor if

- sore mouth symptoms do not improve in 7 days
- irritation, pain or redness persists or worsens
- swelling, rash or fever develops
- cough lasts more than 7 days, comes back, or occurs with fever, or persistent headache. These could be signs of a serious condition.

If pregnant or breast-feeding,

ask a health professional before use.

Keep out of reach of children.

In case of overdose, get medical help or contact a Poison Control Center (1-800-222-1222) right away.

Directions

- do not use more than directed
- adults and children 4 years of age and older: Dissolve 1 lozenge slowly in the mouth. May be repeated every 2 hours as needed or as directed by a doctor or dentist.
- children under 4 years of age: ask a doctor or dentist

Other information

- store between 15-30°C (59-86°F)
- use only if lozenge blister seals are unbroken
- contains FD&C Yellow No.5 (tartrazine) as a color additive

Inactive ingredients

Corn syrup, FD&C yellow no.5, FD&C yellow no.6, honey, lemon oil, propylene glycol, sucrose, tartaric acid, water

Questions

1-800-344-7239

Sucrets.com

PRINCIPAL DISPLAY PANEL

SUCRETS
DYCLONINE / ORAL ANESTHETIC
MENTHOL / COUGH SUPPRESSANT
PECTIN / DRY MOUTH
Honey Lemon
18 LOZENGES